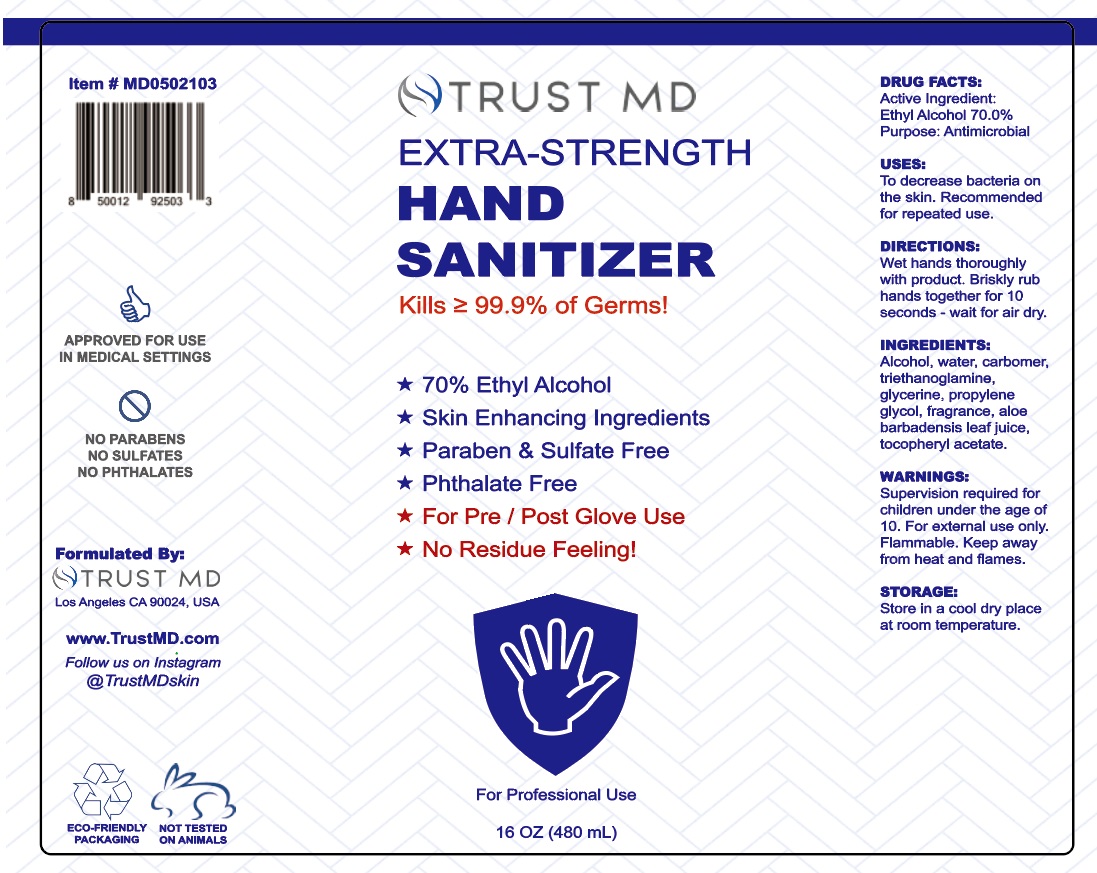 DRUG LABEL: Hand Sanitizer
NDC: 78098-002 | Form: GEL
Manufacturer: GUANGZHOU NODA PHARMACEUTICAL TECHNOLOGY INCORPORATED CO., LTD
Category: otc | Type: HUMAN OTC DRUG LABEL
Date: 20200519

ACTIVE INGREDIENTS: ALCOHOL 70 mL/100 mL
INACTIVE INGREDIENTS: TROLAMINE 0.4 mL/100 mL; ALOE VERA LEAF 2 mL/100 mL; ALPHA-TOCOPHEROL ACETATE 0.5 mL/100 mL; GLYCERIN 2 mL/100 mL; CARBOMER COPOLYMER TYPE A 0.4 mL/100 mL; WATER; PROPYLENE GLYCOL 0.5 mL/100 mL; FRAGRANCE LAVENDER & CHIA F-153480 0.01 mL/100 mL

Water 24.19%, Alcohol 70%, Carbomer 0.4%, Triethanolamine 0.4%, Glycerin 2%, Propylene Glycol 0.5%

,Aloe Barbadensis Leaf Juice 2%, Tocopheryl Acetate 0.5%, Fragrance 0.01%

Active Ingredient(s)

Alcohol Denat 70.0%
Purpose: Antimicrobial

Purpose

Antiseptic, Hand Sanitizer

Use

To decrease bacteria on the skin. Recommended for repeated use.

Warnings

Supervision required for children under the age of 10. For external use only. Flammable. Keep away from heat and flames.

Do not use

- in children less than 2 months of age
- on open skin wounds

When using this product keep out of eyes, ears, and mouth. In case of contact with eyes, rinse eyes thoroughly with water.
Stop use and ask a doctor if irritation or rash occurs. These may be signs of a serious condition.
Keep out of reach of children. If swallowed, get medical help or contact a Poison Control Center right away.

Stop use and ask a doctor if irritation or rash occurs. These may be signs of a serious condition.

Keep out of reach of children. If swallowed, get medical help or contact a Poison Control Center right away.

Directions

Wet hands thoroughly with product. Briskly rub hands together for 10 seconds - wait for air dry.

Other information

Store in a cool dry place at room temperature.

Inactive ingredients

water, carbomer, triethanoglamine, glycerine, propylene glycol, fragrance, aloe barbadensis leaf juice, tocopheryl acetate.

Package Label - Principal Display Panel

480 mL NDC: 78098-001-02